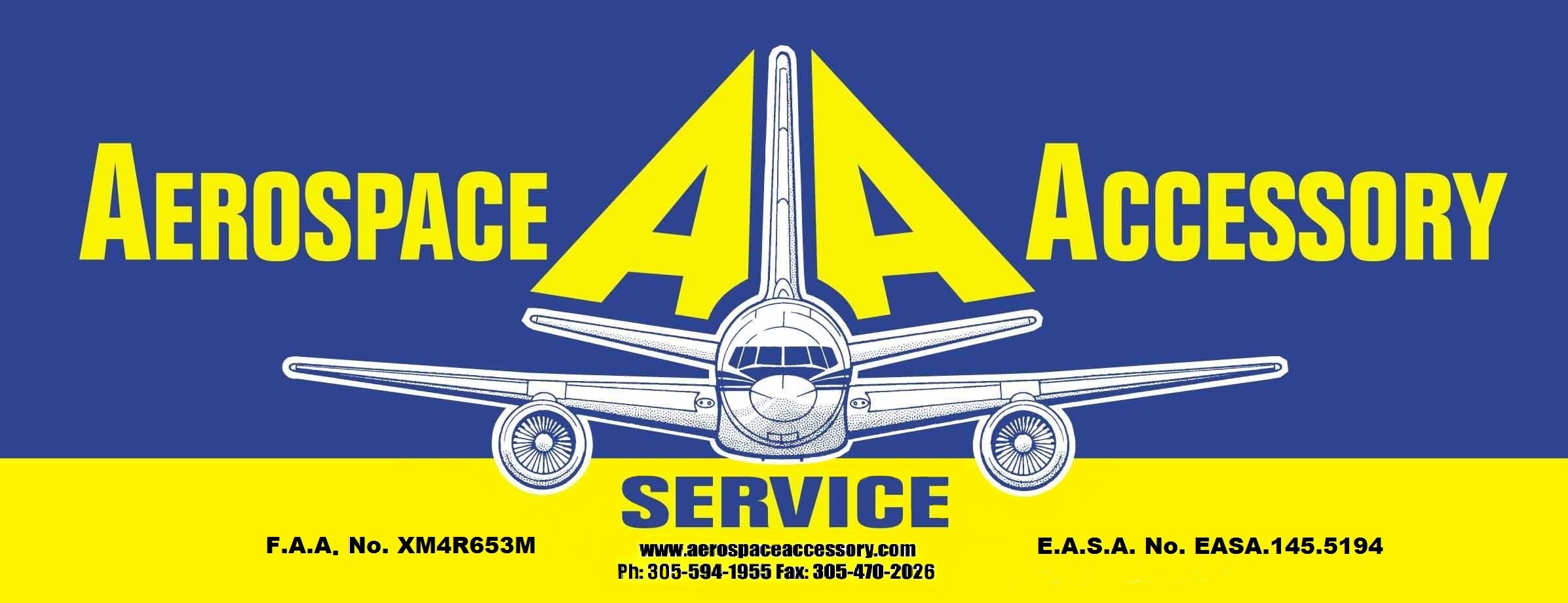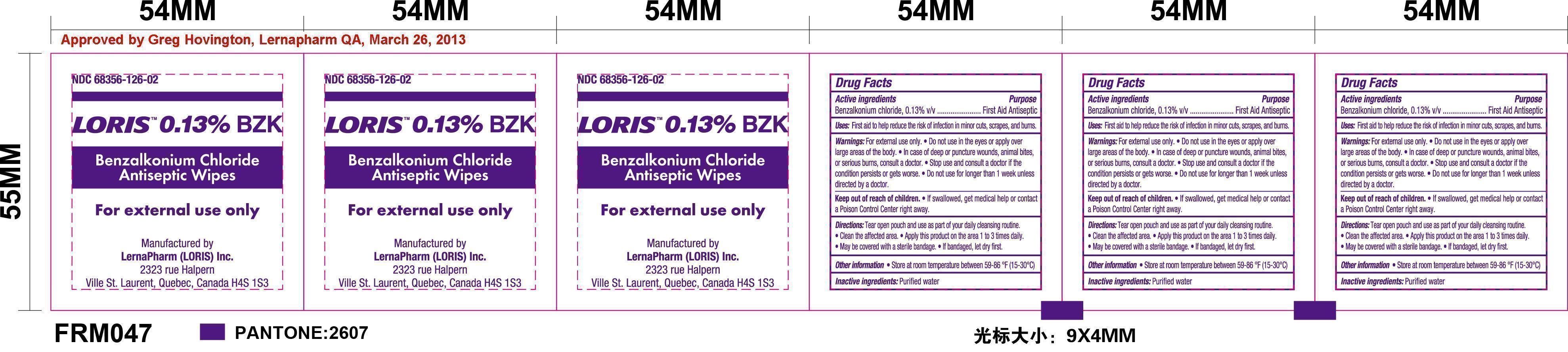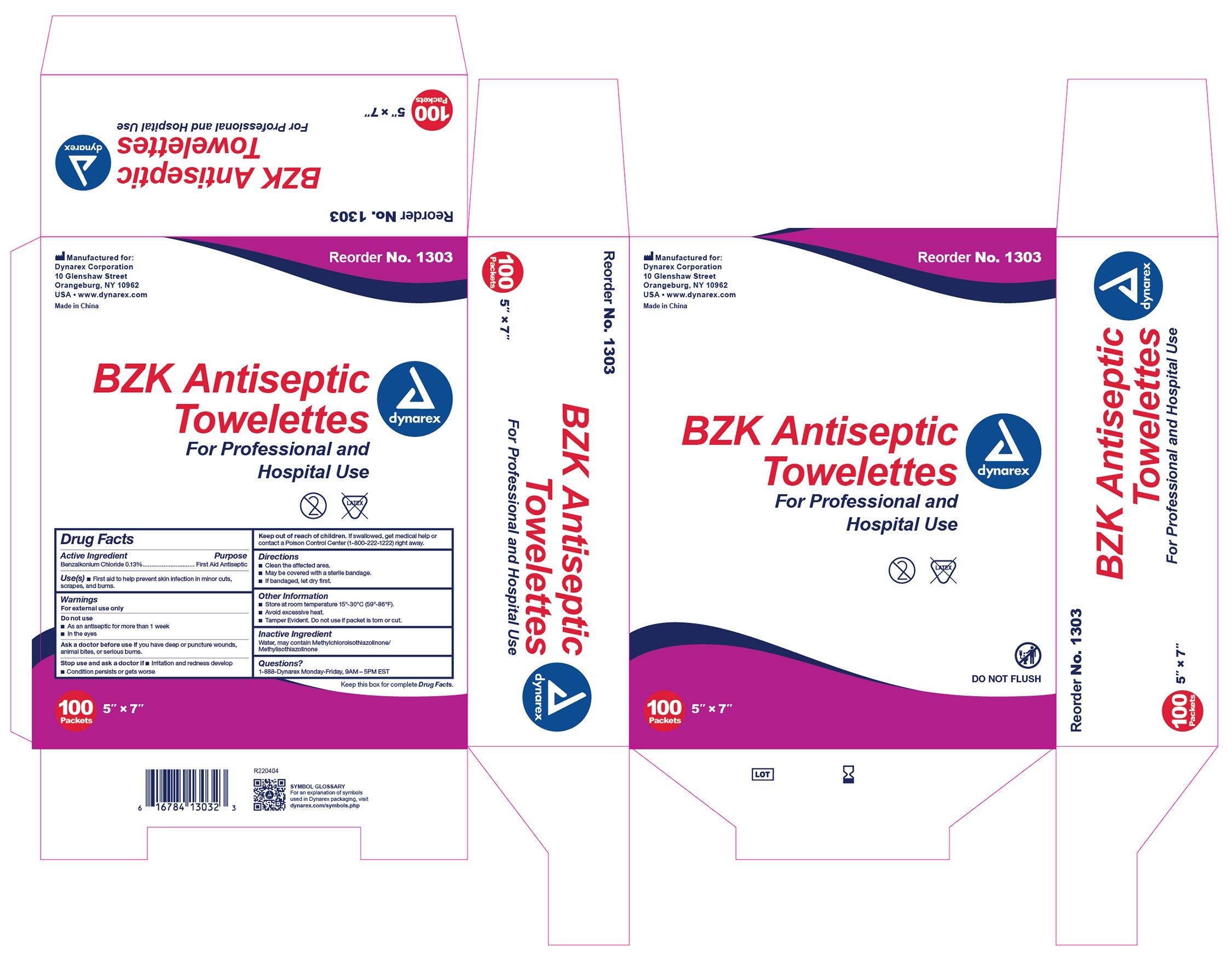 DRUG LABEL: Model AA-2012
NDC: 27860-014 | Form: KIT | Route: TOPICAL
Manufacturer: AEROSPACE ACCESSORY SERVICE
Category: otc | Type: HUMAN OTC DRUG LABEL
Date: 20241001

ACTIVE INGREDIENTS: BENZALKONIUM CHLORIDE 0.13 g/100 g; BENZALKONIUM CHLORIDE 1.3 mg/1 mL
INACTIVE INGREDIENTS: WATER; METHYLCHLOROISOTHIAZOLINONE/METHYLISOTHIAZOLINONE MIXTURE; WATER

Model AA-2012

Antiseptic Wipes Active ingredient

Benzalkonium Chloride 0.13% v/v

Antiseptic Wipes Purpose

First Aid Antiseptic

Antiseptic Wipes Uses

First Aid Antiseptic

Antiseptic Wipes Warnings

For external use only

Do not use it in the eyes or apply over large areas of the body. In case of deep or puncture wounds, animal bites, or serious burns, consult a doctor. Stop use and consult a doctor if the condition persists or gets worse. Do not use it for longer than 1 week unless directed by a doctor.

Antiseptic Wipes Keep out of reach of children

If swallowed, get medical help or contact a Poison Control Center right away.

Antiseptic Wipes Directions

Tear open pouch and use as part of your daily cleansing routine.

Clean the affected area.

Apply this product on the area 1 to 3 times daily.

May be covered with a sterile bandage.

If bandaged, let dry first.

Antiseptic Wipes Other information

- store at room temperature between 59-86 F
- If contact with eyes occurs, flush eyes with water

Antiseptic Wipes Inactive ingredients

Purified water

Antiseptic Wipes Questions

Call 1-866-322-4634, weekdays between 8:00 am and 6:00 pm EST

BZK Pads Active ingredient

Benzalkonium Chloride 0.13% v/v

BZK Pads Purpose

First Aid Antiseptic

BZK Pads Uses

First aid to help prevent skin infection in minor cuts, scrapes and burns

BZK Pads Warnings

For external use only

Do not use

- As an antiseptic for more than 1 week
- In the eyes

Ask a Doctor before use if you have

deep puncture wounds, animal bites, or serious burns

Stop use and ask a doctor if

- irritation or redness develop
- Condition persistor gets worse

Keep out of reach of children

If swallowed get medical help or contact a Poison Control Center (1-800-222-1222) right away

BZK Pads Directions

- Clean the affected area
- May be covered with a sterile bandage
- If bandaged, let dry first

BZK Pads Other Information

- Store at room temperature 15-30C (59-86F)
- Avoid excessive heat
- Temper evident. Do not use if packet is torn or cut

BZK Pads Inactive ingredients

Water, may contain Methylchloroisothiazolinone/Methlylisothiazolinone

BZK Pads Questions

1-800-DYNAREX Monday-Friday 9AM-5PM EST